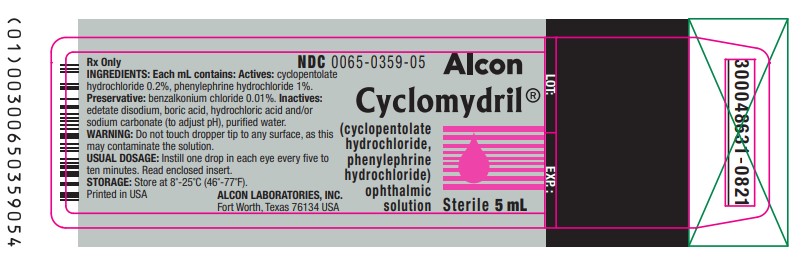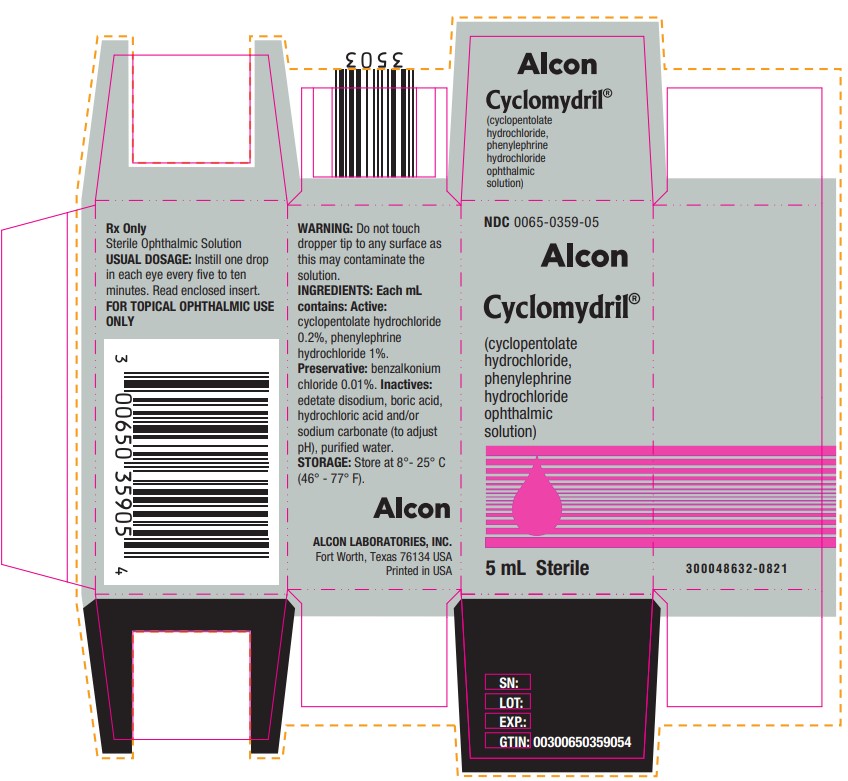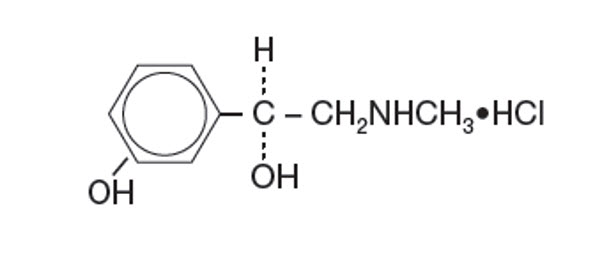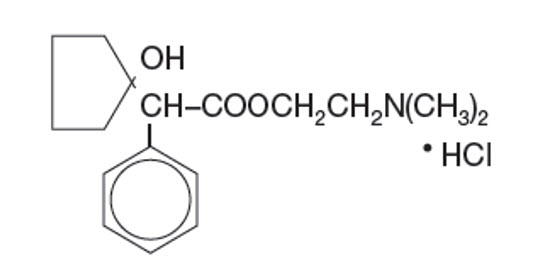 DRUG LABEL: Cyclomydril
NDC: 0065-0359 | Form: SOLUTION/ DROPS
Manufacturer: Alcon Laboratories, Inc.
Category: prescription | Type: HUMAN PRESCRIPTION DRUG LABEL
Date: 20250515

ACTIVE INGREDIENTS: CYCLOPENTOLATE HYDROCHLORIDE 2 mg/1 mL; PHENYLEPHRINE HYDROCHLORIDE 10 mg/1 mL
INACTIVE INGREDIENTS: BENZALKONIUM CHLORIDE; EDETATE DISODIUM; BORIC ACID; HYDROCHLORIC ACID; SODIUM CARBONATE; WATER

Cyclomydril®
(cyclopentolate hydrochloride and phenylephrine hydrochloride ophthalmic solution) Sterile

DESCRIPTION

CYCLOMYDRIL® (cyclopentolate hydrochloride and phenylephrine hydrochloride ophthalmic solution) is a mydriatic prepared as a sterile topical ophthalmic solution. The active ingredients are represented by the chemical structures:

Established Name:
Cyclopentolate Hydrochloride

Chemical Name:
2-(Dimethylamino)ethyl 1 - hydroxy-α-phenylcyclopentaneacetate hydrochloride)

Molecular Formula:
C17H25NO3 • HCl

Molecular Weight:
327.85 g/mol

Established Name:
Phenylephrine Hydrochloride

Chemical Name:
3-hydroxy-α[(methylamino)-methyl]-, Benzenemethanol, hydrochloride (R)-.

Molecular Formula:
C9H13NO2 • HCl

Molecular Weight:
203.67 g/mol

Each mL of CYCLOMYDRIL® (cyclopentolate hydrochloride and phenylephrine hydrochloride ophthalmic solution) contains:
Active: cyclopentolate hydrochloride 0.2%, phenylephrine hydrochloride 1%. Preservative: benzalkonium chloride 0.01%.
Inactives: edetate disodium, boric acid, hydrochloric acid and /or sodium carbonate (to adjust pH), purified water.

CLINICAL PHARMACOLOGY

Cyclopentolate hydrochloride is an anticholinergic drug and phenylephrine hydrochloride is an adrenergic drug. This combination induces mydriasis that is greater than that of either drug alone at its respective concentration. The concentrations of cyclopentolate hydrochloride and phenylephrine hydrochloride have been selected to induce mydriasis with little accompanying cycloplegia. Heavily pigmented irides may require more doses than lightly pigmented irides.

INDICATIONS AND USAGE

For the production of mydriasis.

CONTRAINDICATIONS

Do not use in patients with hypersensitivity to any component of this preparation.

WARNINGS

FOR TOPICAL OPHTHALMIC USE ONLY. NOT FOR INJECTION. There have been reports of serious cardiovascular reactions, including ventricular arrhythmias and myocardial infarctions, in patients using higher concentrations of phenylephrine. These episodes, some fatal, have usually occurred in patients with pre-existing cardiovascular diseases. This preparation may cause central nervous system (CNS) disturbances. This is especially true in younger age groups, but may occur at any age, especially with the stronger solutions. Infants are especially prone to CNS and cardiopulmonary side effects from cyclopentolate.

PRECAUTIONS

General

Caution should be observed when considering use of this medication in the presence of Down's syndrome due to potential increased sensitivity to anticholinergics. This product should be used with caution in patients at risk for angle closure due to the potential to precipitate acute angle closure. Because of the risk of provoking hyperthermia, use with caution in patients, especially children, who may be exposed to elevated environmental temperatures or who are febrile. The use of phenylephrine in the eye may liberate pigment granules from the iris. Mydriatics may produce a transient elevation of intraocular pressure.

Information for Patients

Do not touch dropper tip to any surface, as this may contaminate the solution. Patient should be advised not to drive or engage in hazardous activities while pupils are dilated. Patient may experience sensitivity to light.

Carcinogenesis, Mutagenesis, Impairment of Fertility

There have been no long-term studies done using cyclopentolate hydrochloride and/or phenylephrine hydrochloride in animals to evaluate carcinogenic potential.

Pregnancy

Animal reproduction studies have not been conducted with cyclopentolate hydrochloride and/or phenylephrine hydrochloride. It is also not known whether cyclopentolate hydrochloride and/or phenylephrine hydrochloride can cause fetal harm when administered to a pregnant woman or can affect reproduction capacity. CYCLOMYDRIL® (cyclopentolate hydrochloride and phenylephrine hydrochloride ophthalmic solution) should be given to a pregnant woman only if clearly needed.

Nursing Mothers

It is not known whether these drugs are excreted in human milk. Because many drugs are excreted in human milk, caution should be exercised when CYCLOMYDRIL® (cyclopentolate hydrochloride and phenylephrine hydrochloride ophthalmic solution) is administered to a nursing woman.

Pediatric Use

Use of cyclopentolate has been associated with psychotic reactions and behavioral disturbances in pediatric patients. Increased susceptibility to cyclopentolate has been reported in infants, young children, and in children with spastic paralysis or brain damage. These disturbances include ataxia, incoherent speech, restlessness, hallucinations, hyperactivity, seizures, disorientation as to time and place. Feeding intolerance may follow ophthalmic use of this product in infants. It is recommended that feeding be withheld after administration, and to observe infants closely for at least 30 minutes (see PRECAUTIONS).

Geriatric Use

No overall differences in safety or effectiveness have been observed between elderly and younger patients.

ADVERSE REACTIONS

Ocular

The following ocular adverse experiences have been associated with the use of CYCLOMYDRIL® (cyclopentolate hydrochloride and phenylephrine hydrochloride ophthalmic solution): increased intraocular pressure, burning/irritation upon instillation, photophobia, blurred vision and superficial punctate keratitis.

Nonocular

Use of cyclopentolate hydrochloride has been associated with psychotic reactions and behavioral disturbances in children. These disturbances include ataxia, incoherent speech, restlessness, hallucinations, hyperactivity, seizures, disorientation as to time and place. This drug produces reactions similar to those of other adrenergic and anticholinergic drugs; however, the central nervous system manifestations as noted above are most common. Other manifestations of adrenergic and anticholinergic topical ophthalmic drugs include tachycardia, hyperpyrexia, hypertension, vasodilation, urinary retention, diminished gastrointestinal motility, convulsion, bradycardia, apnea, necrotizing colitis and abdominal distention (in newborns and especially premature infants), skin rash, drowsiness, and decreased secretion in salivary and sweat glands, pharynx, bronchi and nasal passages. Severe manifestations of toxicity include coma, medullary paralysis and death. Systemic toxicity can result from topical application of sympathomimetic drugs: headache, blood pressure elevation, extrasystoles, tachycardia, syncope and cerebrovascular accidents have been reported.

OVERDOSAGE

Excessive dosage may produce behavioral disturbances, tachycardia, hyperpyrexia, hypertension, elevated intraocular pressure, vasodilation, urinary retention, diminished gastrointestinal motility and decreased secretion in salivary and sweat glands, pharynx, bronchi and nasal passages. Pulmonary oedema or cardiac arrest may occur due to phenylephrine toxicity. Severe intoxication is characterized by central nervous system depression, coma, circulatory and respiratory failure, and death.
Patients exhibiting signs of overdosage should receive supportive care and monitoring.

DOSAGE AND ADMINISTRATION

Instill one drop in each eye every five to ten minutes. To minimize systemic absorption, apply pressure over the nasolacrimal sac for two to three minutes following instillation. Observe infants closely for at least 30 minutes.

HOW SUPPLIED

CYCLOMYDRIL® (cyclopentolate hydrochloride and phenylephrine hydrochloride ophthalmic solution) is supplied as a sterile solution in 2 mL and 5 mL, in plastic DROP-TAINER® dispensers.

2 mL NDC 0065-0359-02

5 mL NDC 0065-0359-05

Storage: Store at 8°C to 25°C (46°F - 77°F)

Distributed by:
ALCON LABORATORIES, INC.
6201 South Freeway
Fort Worth, Texas 76134-2099

© 2025 Alcon Inc.

Revised: May 2025.
300065206-1223

PRINCIPAL DISPLAY PANEL

NDC 0065-0359-05
Alcon
Cyclomydril®
(cyclopentolate
hydrochloride,
phenylephrine
hydrochloride
ophthalmic
solution)
5 mL Sterile
Rx Only
Sterile Ophthalmic Solution
USUAL DOSAGE: Instill one drop
in each eye every five to ten
minutes. Read enclosed insert.
FOR TOPICAL OPHTHALMIC USE
ONLY
WARNING: Do not touch
dropper tip to any surface as
this may contaminate the
solution.
INGREDIENTS: Each mL
contains: Active:
cyclopentolate hydrochloride
0.2%, phenylephrine
hydrochloride 1%.
Preservative: benzalkonium
chloride 0.01%. Inactives:
edetate disodium, boric acid,
hydrochloric acid and/or
sodium carbonate (to adjust
pH), purified water.
STORAGE: Store at 8°-25° C
(46° to 77° F).
Alcon
ALCON LABORATORIES, INC.
Fort Worth, Texas 76134 USA
Printed in USA
SN:
LOT:
EXP.:
GTIN: 00300650359054
300048632-0821

NDC 0065-0359-05
Alcon
Cyclomydril®
(cyclopentolate
hydrochloride,
phenylephrine
hydrochloride
ophthalmic
solution)
Sterile 5 mL
Rx Only
INGREDIENTS: Each mL contains: Actives: cyclopentolate
hydrochloride 0.2%, phenylephrine hydrochloride 1%.
Preservative: benzalkonium chloride 0.01%. Inactives:
edetate disodium, boric acid, hydrochloric acid and/or
sodium carbonate (to adjust pH), purified water.
WARNING: Do not touch dropper tip to any surface as this
may contaminate the solution.
USUAL DOSAGE: Instill one drop in each eye every five to
ten minutes. Read enclosed insert.
STORAGE: Store at 8°-25° C (46° to 77° F).
Printed in USA
ALCON LABORATORIES, INC.
Fort Worth, Texas 76134 USA
LOT:
EXP.:
300048631-0821